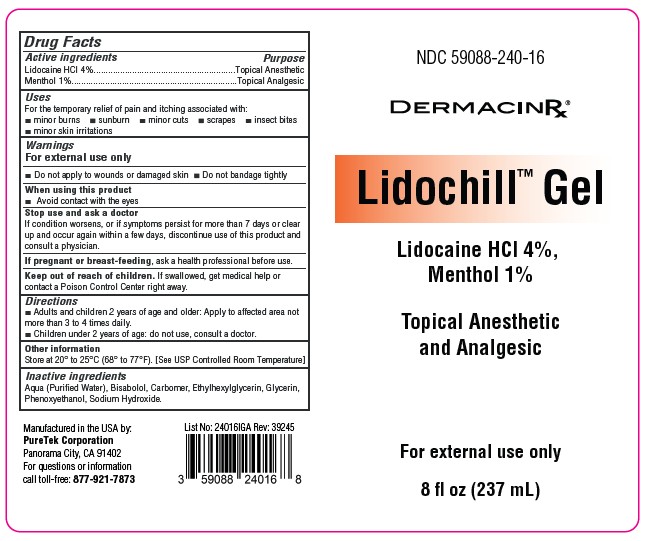 DRUG LABEL: Lidochill(TM) Gel
NDC: 59088-240 | Form: GEL
Manufacturer: PureTek Corporation
Category: otc | Type: HUMAN OTC DRUG LABEL
Date: 20250908

ACTIVE INGREDIENTS: LIDOCAINE HYDROCHLORIDE 40 mg/1 mL; MENTHOL 10 mg/1 mL
INACTIVE INGREDIENTS: CARBOMER; BISABOLOL; ETHYLHEXYLGLYCERIN; SODIUM HYDROXIDE; GLYCERIN; PHENOXYETHANOL; WATER

NDC 59088-240-16
Lidochill™ Gel
(Lidocaine 4% / Menthol 1%)
Topical Anesthetic and Analgesic

Active ingredients (% w/w)

Lidocaine HCL 4%

Menthol 1%

Purposes

Topical Anesthetic (Lidocaine HCL 4%)
Topical Analgesic (Menthol 1%)

Uses

For the temporary relief of pain and itching associated with:
■ minor burns ■ sunburn ■ minor cuts ■ scrapes ■ insect bites
■ minor skin irritations

Warnings

For external use only

DO NOT USE

■ Do not apply to wounds or damaged skin ■ Do not bandage tightly

When using this product

■ Avoid contact with the eyes

Stop use and ask a doctor if

If condition worsens, or if symptoms persist for more than 7 days or clear up and occur again within a few days, discontinue use of this product and consult a physician.

If pregnant or breast-feeding,

ask a health professional before use.

Keep out of reach of children.

If swallowed, get medical help or contact a Poison Control Center right away.

Directions

■ Adults and children 2 years of age and older: Apply to affected area not more than 3 to 4 times daily.
■ Children under 2 years of age: do not use, consult a doctor.

Other information

Store at 20° to 25°C (68° to 77°F). [See USP Controlled Room Temperature]

Inactive ingredients

Aqua (Purified Water), Bisabolol, Carbomer, Ethylhexylglycerin, Glycerin, Phenoxyethanol, Sodium Hydroxide.

PACKAGE LABEL

Manufactured in the USA by:
PureTek Corporation
San Fernando, CA 91340
877-921-7873